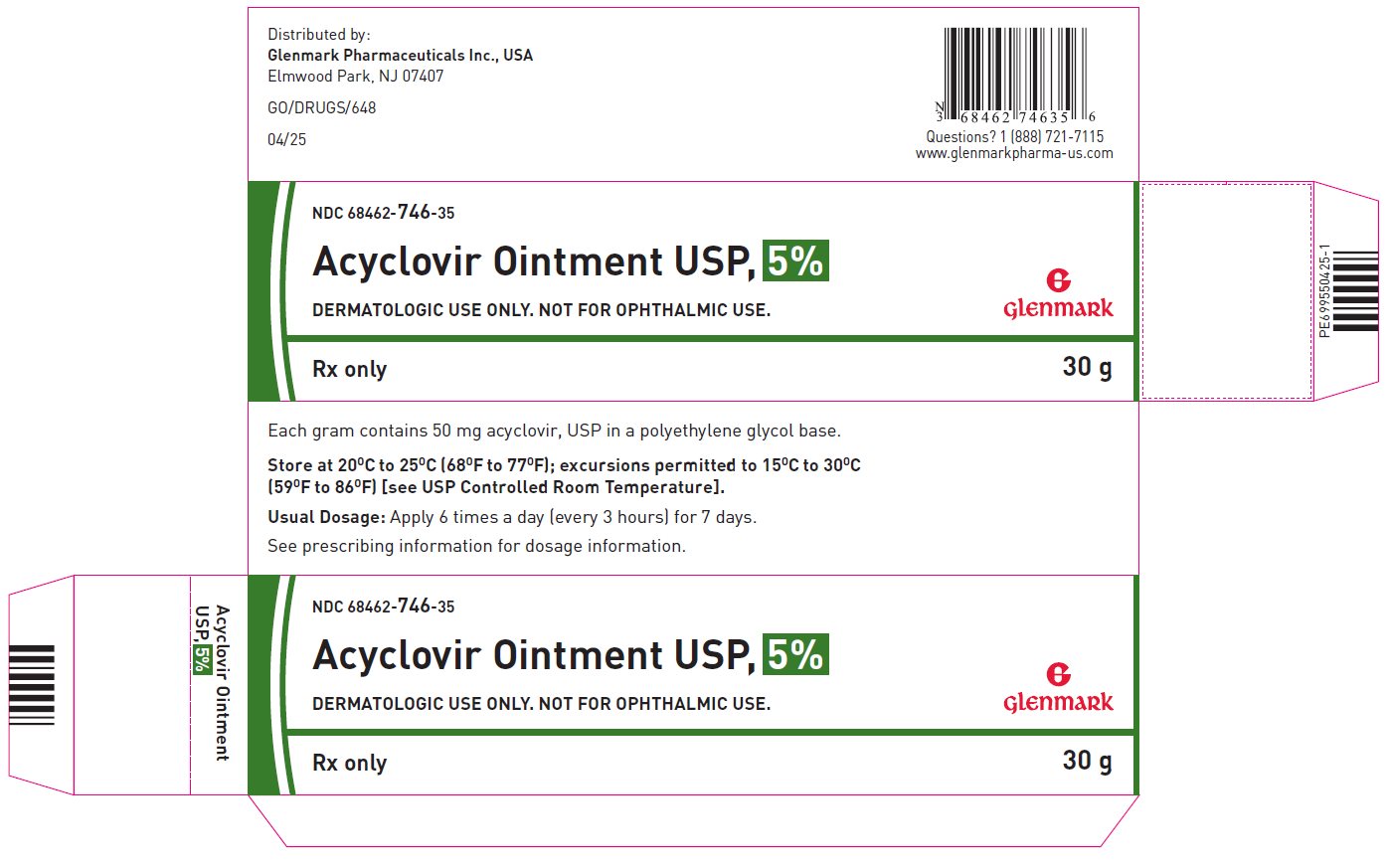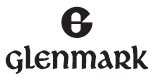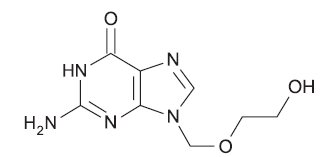 DRUG LABEL: acyclovir
NDC: 68462-746 | Form: OINTMENT
Manufacturer: Glenmark Pharmaceuticals Inc., USA
Category: prescription | Type: HUMAN PRESCRIPTION DRUG LABEL
Date: 20260128

ACTIVE INGREDIENTS: ACYCLOVIR 50 mg/1 g
INACTIVE INGREDIENTS: POLYETHYLENE GLYCOL, UNSPECIFIED

Acyclovir Ointment USP, 5%

DESCRIPTION

Acyclovir is a synthetic nucleoside analogue active against herpes viruses. Acyclovir ointment USP 5% is a formulation for topical administration. Each gram of acyclovir ointment USP, 5% contains 50 mg of acyclovir USP in a polyethylene glycol (PEG) base.

Acyclovir USP is a white to off-white, crystalline powder with the molecular formula C8H11N5O3 and a molecular weight of 225.2 g/mol. The maximum solubility in water at 37°C is 2.5 mg/mL. The pka’s of acyclovir are 2.27 and 9.25.

The chemical name of acyclovir USP is 2-amino-1, 9-dihydro-9- [(2-hydroxyethoxy)methyl]-6H-purin-6-one; it has the following structural formula:

VIROLOGY

Mechanism of Antiviral Action

Acyclovir is a synthetic purine nucleoside analogue with in vitro and in vivo inhibitory activity against herpes simplex virus types 1 (HSV-1), 2 (HSV-2), and varicella-zoster virus (VZV).

The inhibitory activity of acyclovir is highly selective due to its affinity for the enzyme thymidine kinase (TK) encoded by HSV and VZV. This viral enzyme converts acyclovir into acyclovir monophosphate, a nucleotide analogue. The monophosphate is further converted into diphosphate by cellular guanylate kinase and into triphosphate by a number of cellular enzymes. In vitro, acyclovir triphosphate stops replication of herpes viral DNA. This is accomplished in 3 ways: 1) competitive inhibition of viral DNA polymerase, 2) incorporation into and termination of the growing viral DNA chain, and 3) inactivation of the viral DNA polymerase. The greater antiviral activity of acyclovir against HSV compared to VZV is due to its more efficient phosphorylation by the viral TK.

Antiviral Activities

The quantitative relationship between the in vitro susceptibility of herpes viruses to antivirals and the clinical response to therapy has not been established in humans, and virus sensitivity testing has not been standardized. Sensitivity testing results, expressed as the concentration of drug required to inhibit by 50% the growth of virus in cell culture (IC50), vary greatly depending upon a number of factors. Using plaque-reduction assays, the IC50 against herpes simplex virus isolates ranges from 0.02 to 13.5 mcg/mL for HSV-1 and from 0.01 to 9.9 mcg/mL for HSV-2. The IC50 for acyclovir against most laboratory strains and clinical isolates of VZV ranges from 0.12 to 10.8 mcg/mL. Acyclovir also demonstrates activity against the Oka vaccine strain of VZV with a mean IC50 of 1.35 mcg/mL.

Drug Resistance

Resistance of HSV and VZV to acyclovir can result from qualitative or quantitative changes in the viral TK and/or DNA polymerase. Clinical isolates of HSV and VZV with reduced susceptibility to acyclovir have been recovered from immunocompromised patients, especially with advanced HIV infection. While most of the acyclovir-resistant mutants isolated thus far from immunocompromised patients have been found to be TK-deficient mutants, other mutants involving the viral TK gene (TK partial and TK altered) and DNA polymerase have been isolated. TK-negative mutants may cause severe disease in infants and immunocompromised adults. The possibility of viral resistance to acyclovir should be considered in patients who show poor clinical response during therapy.

CLINICAL PHARMACOLOGY

Two clinical pharmacology studies were performed with acyclovir ointment 5% in immunocompromised adults at risk of developing mucocutaneous Herpes simplex virus infections or with localized varicella-zoster infections. These studies were designed to evaluate the dermal tolerance, systemic toxicity, and percutaneous absorption of acyclovir.

In 1 of these studies, which included 16 inpatients, the complete ointment or its vehicle were randomly administered in a dose of 1-cm strips (25 mg acyclovir) 4 times a day for 7 days to an intact skin surface area of 4.5 square inches. No local intolerance, systemic toxicity, or contact dermatitis were observed. In addition, no drug was detected in blood and urine by radioimmunoassay (sensitivity, 0.01 mcg/mL).

The other study included 11 patients with localized varicella-zoster infections. In this uncontrolled study, acyclovir was detected in the blood of 9 patients and in the urine of all patients tested. Acyclovir levels in plasma ranged from <0.01 to 0.28 mcg/mL in 8 patients with normal renal function, and from <0.01 to 0.78 mcg/mL in 1 patient with impaired renal function. Acyclovir excreted in the urine ranged from <0.02% to 9.4% of the daily dose. Therefore, systemic absorption of acyclovir after topical application is minimal.

CLINICAL TRIALS

In clinical trials of initial genital herpes infections, acyclovir ointment 5% has shown a decrease in healing time and, in some cases, a decrease in duration of viral shedding and duration of pain. In studies in immunocompromised patients mainly with herpes labialis, there was a decrease in duration of viral shedding and a slight decrease in duration of pain.

In studies of recurrent genital herpes and of herpes labialis in nonimmunocompromised patients, there was no evidence of clinical benefit; there was some decrease in duration of viral shedding.

INDICATIONS AND USAGE

Acyclovir ointment 5% is indicated in the management of initial genital herpes and in limited non-life-threatening mucocutaneous Herpes simplex virus infections in immunocompromised patients.

CONTRAINDICATIONS

Acyclovir ointment 5% is contraindicated in patients who develop hypersensitivity to the components of the formulation.

WARNINGS

Acyclovir ointment 5% is intended for cutaneous use only and should not be used in the eye.

PRECAUTIONS

General

The recommended dosage, frequency of applications, and length of treatment should not be exceeded (see DOSAGE AND ADMINISTRATION). There are no data to support the use of acyclovir ointment 5% to prevent transmission of infection to other persons or prevent recurrent infections when applied in the absence of signs and symptoms. Acyclovir ointment 5% should not be used for the prevention of recurrent HSV infections. Although clinically significant viral resistance associated with the use of acyclovir ointment 5% has not been observed, this possibility exists.

Drug Interactions

Clinical experience has identified no interactions resulting from topical or systemic administration of other drugs concomitantly with acyclovir ointment 5%.

Carcinogenesis, Mutagenesis, Impairment of Fertility

Systemic exposure following topical administration of acyclovir is minimal. Dermal carcinogenicity studies were not conducted. Results from the studies of carcinogenesis, mutagenesis, and fertility are not included in the full prescribing information for acyclovir ointment 5% due to the minimal exposures of acyclovir that result from dermal application.

Pregnancy

Teratogenic Effects: Pregnancy Category B. Acyclovir was not teratogenic in the mouse, rabbit, or rat at exposures greatly in excess of human exposure. There are no adequate and well-controlled studies of systemic acyclovir in pregnant women. A prospective epidemiologic registry of acyclovir use during pregnancy was established in 1984 and completed in April 1999. There were 749 pregnancies followed in women exposed to systemic acyclovir during the first trimester of pregnancy resulting in 756 outcomes. The occurrence rate of birth defects approximates that found in the general population. However, the small size of the registry is insufficient to evaluate the risk for less common defects or to permit reliable or definitive conclusions regarding the safety of acyclovir in pregnant women and their developing fetuses. Systemic acyclovir should be used during pregnancy only if the potential benefit justifies the potential risk to the fetus.

Nursing Mothers

It is not known whether topically applied acyclovir is excreted in breast milk. Systemic exposure following topical administration is minimal. After oral administration of acyclovir, acyclovir concentrations have been documented in breast milk in 2 women and ranged from 0.6 to 4.1 times the corresponding plasma levels. These concentrations would potentially expose the nursing infant to a dose of acyclovir up to 0.3 mg/kg per day. Nursing mothers who have active herpetic lesions near or on the breast should avoid nursing.

Geriatric Use

Clinical studies of acyclovir ointment did not include sufficient numbers of subjects aged 65 and over to determine whether they respond differently from younger subjects. Other reported clinical experience has not identified differences in responses between the elderly and younger patients. Systemic absorption of acyclovir after topical administration is minimal (see CLINICAL PHARMACOLOGY).

Pediatric Use

Safety and effectiveness in pediatric patients have not been established.

ADVERSE REACTIONS

In the controlled clinical trials, mild pain (including transient burning and stinging) was reported by about 30% of patients in both the active and placebo arms; treatment was discontinued in 2 of these patients. Local pruritus occurred in 4% of these patients. In all studies, there was no significant difference between the drug and placebo group in the rate or type of reported adverse reactions nor were there any differences in abnormal clinical laboratory findings.

Observed During Clinical Practice

Based on clinical practice experience in patients treated with acyclovir ointment in the US, spontaneously reported adverse events are uncommon. Data are insufficient to support an estimate of their incidence or to establish causation. These events may also occur as part of the underlying disease process. Voluntary reports of adverse events that have been received since market introduction include:

General: Edema and/or pain at the application site.
Skin: Pruritus, rash.

OVERDOSAGE

Overdosage by topical application of acyclovir ointment 5% is unlikely because of limited transcutaneous absorption (see CLINICAL PHARMACOLOGY).

DOSAGE AND ADMINISTRATION

Apply sufficient quantity to adequately cover all lesions every 3 hours, 6 times per day for 7 days. The dose size per application will vary depending upon the total lesion area but should approximate a one-half inch ribbon of ointment per 4 square inches of surface area. A finger cot or rubber glove should be used when applying acyclovir ointment to prevent autoinoculation of other body sites and transmission of infection to other persons. Therapy should be initiated as early as possible following onset of signs and symptoms.

HOW SUPPLIED

Each gram of acyclovir ointment USP, 5% contains 50 mg acyclovir USP in a polyethylene glycol base. Acyclovir ointment USP, 5% is a white to off-white translucent ointment. It is supplied as follows:

NDC 68462-746-17 15 gram tubes (1 tube per carton)
  NDC 68462-746-35 30 gram tubes (1 tube per carton)

Store at 20°C to 25°C (68°F to 77°F); excursions permitted to 15°C to 30°C (59°F to 86°F) [See USP Controlled Room Temperature].

Distributed by:

Glenmark Pharmaceuticals Inc., USA
Elmwood Park, NJ 07407

Questions? 1 (888) 721-7115
www.glenmarkpharma-us.com

April 2025